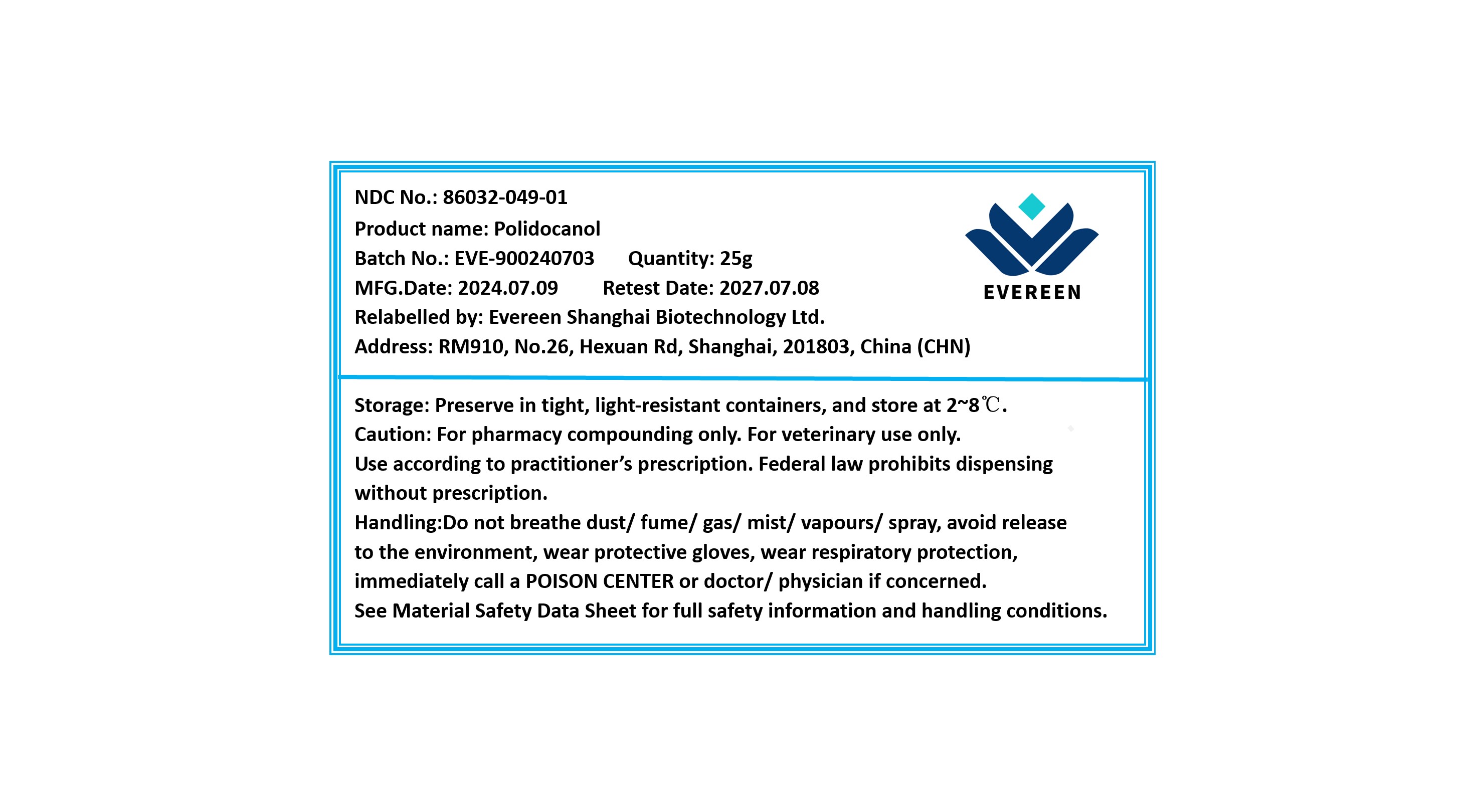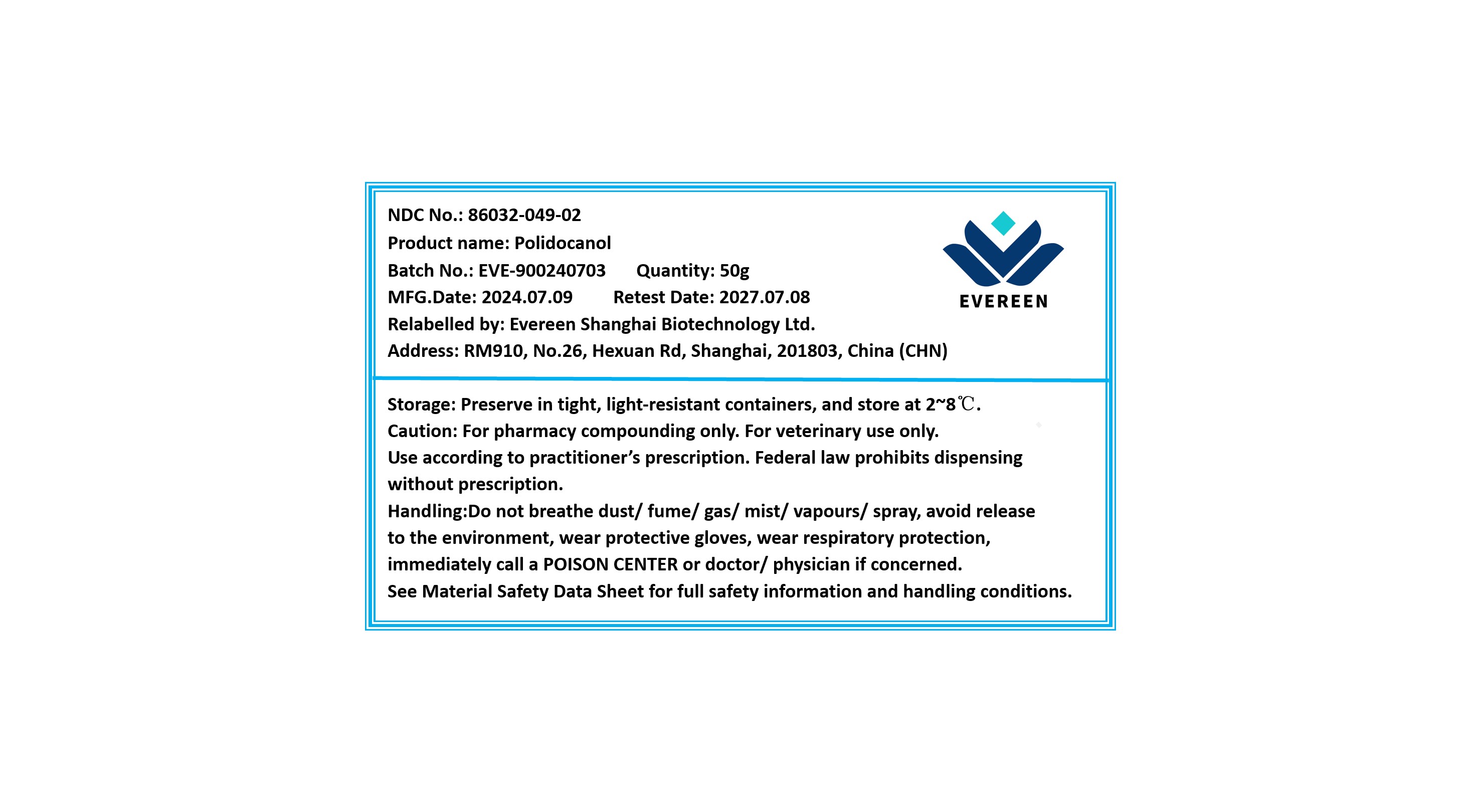 DRUG LABEL: Polidocanol
NDC: 86032-049 | Form: cream
Manufacturer: Evereen Shanghai Biotechnology Ltd.
Category: other | Type: BULK INGREDIENT - ANIMAL DRUG
Date: 20250530

ACTIVE INGREDIENTS: POLIDOCANOL 1 g/1 g

Polidocanol